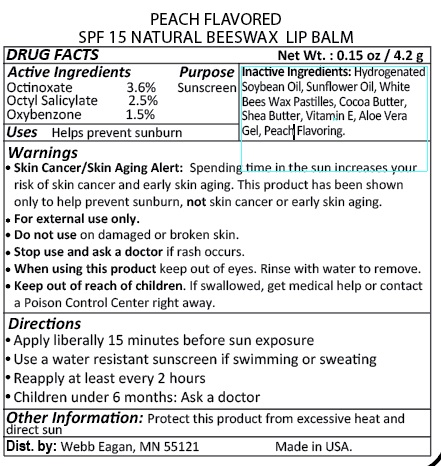 DRUG LABEL: Lip Balm Peach Flavored
NDC: 70445-241 | Form: LIPSTICK
Manufacturer: Webb Business Promotions
Category: otc | Type: HUMAN OTC DRUG LABEL
Date: 20170303

ACTIVE INGREDIENTS: OCTINOXATE 3.6 g/1 g; OCTISALATE 2.5 g/1 g; OXYBENZONE 1.5 g/1 g
INACTIVE INGREDIENTS: HYDROGENATED SOYBEAN OIL; COCOA BUTTER; SHEA BUTTER; ALOE VERA LEAF; .ALPHA.-TOCOPHEROL; WHITE WAX; SUNFLOWER OIL

SPF 15 Lip Balm Peach Flavored

Purpose

Sun Screen

Drug Facts

Octinoxate 3.6%

Octisalate 2.5%

Benzophenone 1.5%

Inactive Ingredients

Hydrogenated Soybean Oil, Sunflower Oil, White Beeswax Pastilles, Cocoa Butter, Shea Butter, Vitamin E, Aloe Vera Gel, Peach Flavoring.

Warnings

- Skin Cancer/Skin Aging Alert: Spending too much time in the sun increases your risk of skin cancer and early skin aging. This product has been shown to only help prevent sunburn, not skin cancer or early skin aging.
- For external use only.
- Do not use on damaged or broken skin.
- Stop use and ask doctor if rash occurs.
- When using this product keep out of eyes.
- Keep out of reach of children. If swallowed get medical help or contact posion control center right away.

Directions

- Apply liberally 15 minutes before sun exposure
- Use a water resistant sunscreen if swimming or sweating
- Reapply every 2 hours
- Children under 6 months : Ask a doctor

Storage and Handling Information

Protect this product from excessive heat and direct sun